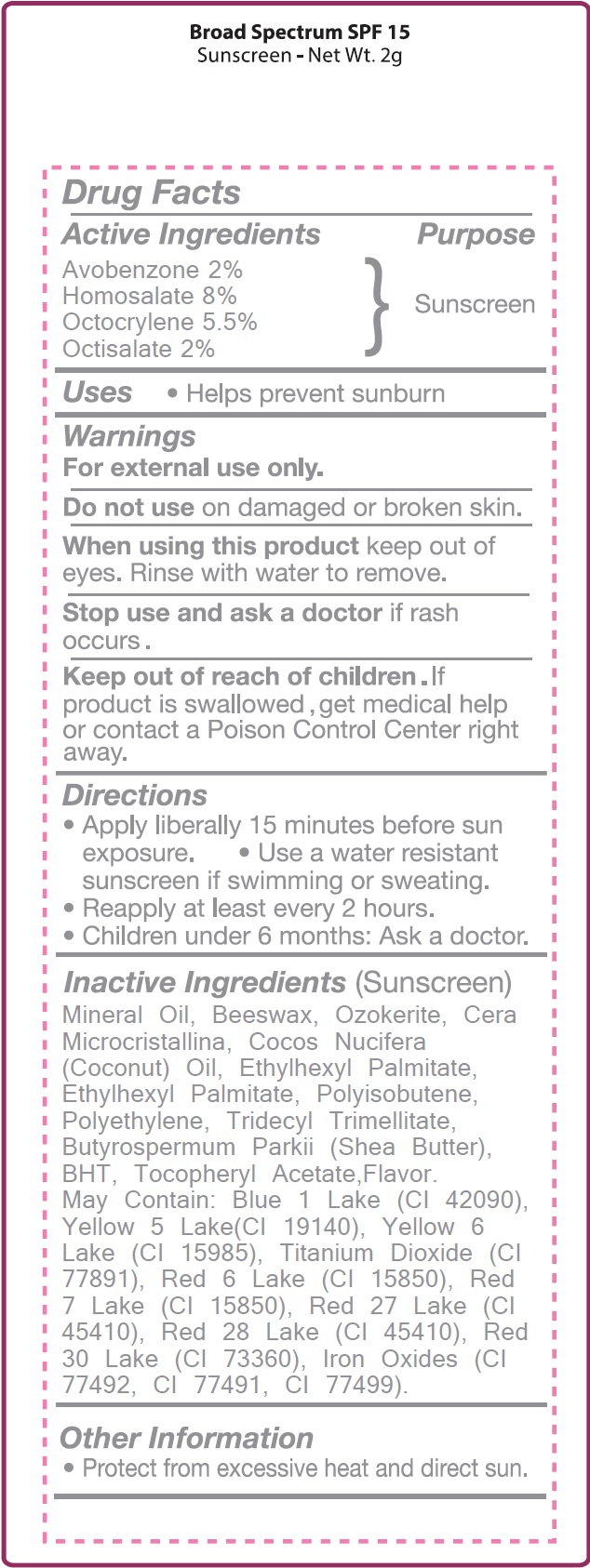 DRUG LABEL: SPF15 Sunscreen
NDC: 70412-212 | Form: STICK
Manufacturer: Zhejiang Ayan Biotech Co.,Ltd.
Category: otc | Type: HUMAN OTC DRUG LABEL
Date: 20231106

ACTIVE INGREDIENTS: AVOBENZONE 20 mg/1 g; HOMOSALATE 80 mg/1 g; OCTOCRYLENE 55 mg/1 g; OCTISALATE 20 mg/1 g
INACTIVE INGREDIENTS: MINERAL OIL; YELLOW WAX; COCONUT OIL; ETHYLHEXYL PALMITATE; HIGH DENSITY POLYETHYLENE; TRIDECYL TRIMELLITATE; SHEA BUTTER; BUTYLATED HYDROXYTOLUENE; METHYL SALICYLATE

SPF15 Sunscreen

Active Ingredients

Homosalate 8% Octocrylene 5.5% Avobenzone 2% Octisalate 2%

Purpose

Sunscreen

Uses

- Helps prevent sunburn

Warnings

For external use only.

Do not use

on damaged or broken skin.

When using this product

keep out of eyes. Rinse with water to remove.

Stop use and ask a doctor

if rash occurs.

Keep out of reach of children.

If product is swallowed, get medical help or contact a Poison Control Center right away.

Directions

- Apply liberally 15 minutes before sun exposure.
- Use a water resistant sunscreen if swimming or sweating.
- Reapply at least every 2 hours.
- Children under 6 months: Ask a doctor.

(Sunscreen) Inactive Ingredients

Mineral Oil, Beeswax, Ozokerite, Cera Microcristallina, Cocos Nucifera (Coconut) Oil, Ethylhexyl Palmitate, Ethylhexyl Palmitate, Polyisobutene, Polyethylene, Tridecyl Trimellitate, Butyrospermum Parkii (Shea Butter), BHT, Tocopheryl Acetate,Flavor. May Contain: Blue 1 Lake (CI 42090), Yellow 5 Lake(CI 19140), Yellow 6 Lake (CI 15985), Titanium Dioxide (CI 77891), Red 6 Lake (CI 15850), Red 7 Lake (CI 15850), Red 27 Lake (CI 45410), Red 28 Lake (CI 45410), Red 30 Lake (CI 73360), Iron Oxides (CI 77492, CI 77491, CI 77499).

Other Information

- Protect from excessive heat and direct sun.